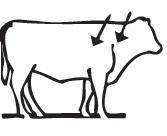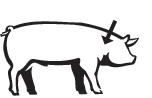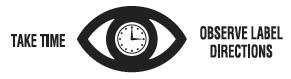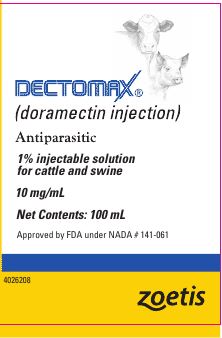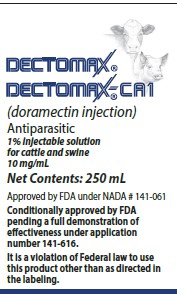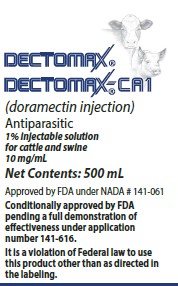 DRUG LABEL: Dectomax
NDC: 54771-5438 | Form: INJECTION, SOLUTION
Manufacturer: Zoetis Inc.
Category: animal | Type: OTC ANIMAL DRUG LABEL
Date: 20251103

ACTIVE INGREDIENTS: DORAMECTIN 10 mg/1 mL

DECTOMAX®
DECTOMAX®-CA1
(doramectin Injection)

Antiparasitic

1% injectable solution for cattle and swine

10 mg/mL

Approved by FDA under NADA # 141-061

Conditionally approved by FDA pending a full demonstration of effectiveness under application number 141-616.

It is a violation of Federal law to use this product other than as directed in the labeling.

PRODUCT DESCRIPTION

Dectomax/Dectomax-CA1 is a ready-to-use, colorless to pale yellow, sterile solution containing 1% w/v doramectin (10 mg/mL). In cattle, Dectomax/Dectomax-CA1 is formulated to deliver the recommended dosage (200 mcg/kg of body weight) when given by subcutaneous (SC) or intramuscular (IM) injection at the rate of 1 mL/110 lb of body weight. In swine, Dectomax is formulated to deliver the recommended dosage (300 mcg/kg of body weight) when given by IM injection at the rate of 1 mL/75 lb of body weight.

PRODUCT CHARACTERISTICS

Dectomax injectable solution is a highly active, broad-spectrum parasiticide for parenteral administration to cattle and swine. It contains doramectin, a novel fermentation-derived macrocyclic lactone. Doramectin is isolated from fermentations of selected strains derived from the soil organism Streptomyces avermitilis.

A primary mode of action of macrocyclic lactones is to modulate chloride ion channel activity in the nervous system of nematodes and arthropods. Macrocyclic lactones bind to receptors that increase membrane permeability to chloride ions. This inhibits the electrical activity of nerve cells in nematodes and muscle cells in arthropods and causes paralysis and death of the parasites. In mammals, the neuronal receptors to which macrocyclic lactones bind are localized within the central nervous system (CNS), a site reached by only negligible concentrations of doramectin.

One dose of Dectomax injectable solution effectively treats and controls a wide range of roundworm and arthropod parasites that impair the health and productivity of cattle and swine.

Studies have demonstrated the safety margin of Dectomax injection in cattle and swine. In USA trials, no toxic signs were seen in cattle given up to 25 times the recommended dose, or in swine given up to 10 times the recommended dose. Studies also demonstrated safety in neonatal calves and piglets treated with up to 3 times the recommended dose. In males (bulls and boars) and females (cows and sows during folliculogenesis, implantation, organogenesis, and through gestation), a dose 3 times the recommended dose had no effect on breeding performance.

PRODUCT INDICATIONS

Cattle

Dectomax is indicated for the treatment and control of the following harmful species of gastrointestinal roundworms, lungworms, eyeworms, grubs (see PRECAUTIONS), sucking lice (see PRECAUTIONS), and mange mites. Consult your veterinarian for assistance in the diagnosis, treatment, and control of parasitism.

Gastrointestinal Roundworms
(adults and fourth stage larvae)
Ostertagia ostertagi (including inhibited larvae)
O. lyrata
Haemonchus placei
Trichostrongylus axei
T. colubriformis
T. longispicularis [adults]
Cooperia oncophora
C. pectinata
C. punctata
C. surnabada (syn. mcmasteri)
Bunostomum phlebotomum
Strongyloides papillosus
Oesophagostomum radiatum Trichuris spp.

Lungworms (adults and fourth stage larvae)
Dictyocaulus viviparus
Eyeworms (adults)
Thelazia spp.
Grubs (parasitic stages)
Hypoderma bovis
H. lineatum
Sucking Lice
Haematopinus eurysternus
Linognathus vituli
Solenopotes capillatus
Mange Mites
Psoroptes bovis
Sarcoptes scabiei

^1 Adults

Dectomax has been proved to effectively control infections and to protect cattle from reinfection with Cooperia oncophora and Haemonchus placei for 14 days, Ostertagia ostertagi for 21 days, and C. punctata, Oesophagostomum radiatum, and Dictyocaulus viviparus for 28 days after treatment.

Dectomax-CA1 is indicated for prevention and treatment of infestations caused by larvae of Cochliomyia hominivorax (myiasis), and prevention of reinfestation for 21 day.

Swine

Dectomax is indicated for the treatment and control of the following species of gastrointestinal roundworms, lungworms, kidney worms, sucking lice (see PRECAUTIONS), and mange mites. Consult your veterinarian for assistance in the diagnosis, treatment, and control of parasitism.

Gastrointestinal Roundworms
(adults and fourth stage larvae)
Ascaris suum
Oesophagostomum dentatum
Oesophagostomum quadrispinulatum [adults]
Strongyloides ransomi
Hyostrongylus rubidus

Lungworms (adults)
Metastrongylus spp.
Kidney Worms (adults)
Stephanurus dentatus
Mange Mites (adults and immature stages)
Sarcoptes scabiei var. suis
Sucking Lice (adults and immature stages)
Haematopinus suis

DOSAGE

Cattle

Administer Dectomax/Dectomax-CA1 at the recommended dosage of 200 mcg doramectin per kg (91 mcg/lb) of body weight. Each mL of Dectomax/Dectomax-CA1 contains 10 mg of doramectin and 218 mg of ethyl oleate in a sesame oil vehicle, sufficient to treat 110 lb (50 kg) of body weight.

Body Weight (lb) | Dose (mL)
110 | 1
220 | 2
330 | 3
440 | 4
550 | 5
660 | 6
770 | 7
880 | 8
990 | 9
1,100 | 10

Swine

Administer Dectomax at the recommended dosage of 300 mcg doramectin per kg (136 mcg/lb) of body weight. Each mL of Dectomax contains 10 mg of doramectin and 218 mg of ethyl oleate in a sesame oil vehicle, sufficient to treat 75 lb (34 kg) of body weight.

Body Weight (lb) | Dose (mL)
15 | 0.2
30 | 0.4
45 | 0.6
60 | 0.8
75 | 1.0
150 | 2.0
225 | 3.0
300 | 4.0
375 | 5.0
450 | 6.0

Do not underdose. Ensure each animal receives a complete dose based on a current body weight. Underdosing may result in ineffective treatment, and encourage the development of parasite resistance.

RECOMMENDED TREATMENT PROGRAM FOR SWINE

To effectively initiate control of mange and sucking lice in swine, it is important to treat all animals in the herd. After initial treatment, use Dectomax regularly as follows:

Breeding Animals:

Sows: Treat 7–14 days prior to farrowing to minimize exposure of piglets to mites and sucking lice.

Gilts: Treat 7–14 days prior to breeding. Treat 7–14 days prior to farrowing.

Boars: Treat a minimum of 2 times per year.

Feeder Pigs

Treat any new feeder pigs upon arrival at farm or before placement in clean quarters.

Weaners, Growers, Finishers

Weaners and grow-out/finisher pigs should be treated before placement in clean quarters.

For effective mange elimination, care must be taken to prevent reinfestation from exposure to untreated animals or contaminated facilities.

ADMINISTRATION

Dry, sterile equipment and aseptic procedures should be used when withdrawing and administering Dectomax/Dectomax-CA1. For multiple treatments either automatic injection equipment or an aspirating needle should be used.

Cattle

Administer Dectomax/Dectomax-CA1 by SC or IM route. Injections should be made using a 16 gauge needle for adult cattle or an 18 gauge needle for young animals. Needles 1/2–3/4" in length are suggested for SC administration. A 1-1/2" needle is suggested for IM administration. SC injections should be administered under the loose skin in front of or behind the shoulder. IM injections should be administered into the muscular region of the neck. Beef Quality Assurance guidelines recommend SC administration as the preferred route.

Swine

Administer Dectomax by the IM route. Inject in the neck region using an 18 gauge × 1" needle for young animals; a 16 gauge × 1-1/2" needle for sows and boars. To accurately meter doses administered to piglets, use of a tuberculin syringe and 20 gauge × 1" needle is recommended.

WARNINGS

Not for human use. Keep out of reach of children. The safety data sheet (SDS) contains more detailed occupational safety information. To report adverse effects in users, to obtain more information, or to obtain an SDS, call 1-888-963-8471.

OTHER WARNINGS

Parasite resistance may develop to any dewormer, and has been reported for most classes of dewormers. Treatment with a dewormer used in conjunction with parasite management practices appropriate to the geographic area and the animal(s) to be treated may slow the development of parasite resistance. Fecal examinations or other diagnostic tests and parasite management history should be used to determine if the product is appropriate for the herd prior to the use of any dewormer. Following the use of any dewormer, effectiveness of treatment should be monitored (for example, with the use of a fecal egg count reduction test or another appropriate method). A decrease in a drug's effectiveness over time as calculated by fecal egg count reduction tests may indicate the development of resistance to the dewormer administered. Your parasite management plan should be adjusted accordingly based on regular monitoring.

RESIDUE WARNINGS

Cattle: Do not slaughter for human consumption within 35 days of treatment. Not for use in female dairy cattle 20 months of age or older. A withdrawal period has not been established for this product in preruminating calves. Do not use in calves to be processed for veal. Swine: Do not slaughter for human consumption within 24 days of treatment.

PRECAUTIONS

Dectomax/Dectomax-CA1 has been developed specifically for use in cattle and swine only. This product should not be used in other animal species as severe adverse reactions, including fatalities in dogs, may result.

For SC injection in cattle only. For IM injection in swine and cattle. This product is approved for the treatment and control of sucking lice. For treatment of biting lice in cattle, use of Dectomax Pour-On is recommended.

Dectomax is highly effective against all stages of cattle grubs. However, proper timing of treatment is important. For most effective results, cattle should be treated as soon as possible after the end of the heel fly (warble) season.

Destruction of Hypoderma larvae (cattle grubs) at the period when these grubs are in vital areas may cause undesirable host-parasite reactions including the possibility of fatalities. Killing H. lineatum when it is in the tissue surrounding the gullet may cause bloat; killing H. bovis when it is in the vertebral canal may cause staggering or paralysis. These reactions are not specific to treatment with Dectomax, but can occur with any successful treatment of grubs. Cattle should be treated either before or after these stages of grub development. Consult your veterinarian concerning the proper time for treatment.

Cattle treated with Dectomax after the end of the heel fly season may be re-treated with Dectomax during the winter for internal parasites, mange mites, or sucking lice, without danger of grub-related reactions. A planned parasite control program is recommended.

ENVIRONMENTAL SAFETY

Studies indicate that when doramectin comes in contact with the soil, it readily and tightly binds to the soil and becomes inactive over time. Free doramectin may adversely affect fish and certain aquatic organisms. Do not permit water runoff from feedlots to enter streams or ponds. Do not contaminate water by direct application or by the improper disposal of drug containers. Dispose of containers in an approved landfill or by incineration.

As with other avermectins, doramectin is excreted in the dung of treated animals and can inhibit the reproduction and growth of pest and beneficial insects that use dung as a source of food and for reproduction. The magnitude and duration of such effects are species and life-cycle specific.

When used according to label directions, the product is not expected to have an adverse impact on populations of dung-dependent insects.

STORAGE AND HANDLING

Store Below 30°C (86°F)
Use this product within 90 days of the first puncture and puncture a maximum of 25 times. If more than 25 punctures are anticipated, the use of automatic injection equipment or a repeater syringe is recommended. When using a draw-off spike or needle with bore diameter larger than 16 gauge, discard any product remaining in the vial immediately after use.

HOW SUPPLIED

Dectomax is available in 100 mL multi-dose, rubber capped glass vial.
Dectomax/Dectomax-CA1 is available in 250 mL and 500 mL multi-dose, rubber capped glass vials.

Approved by FDA under NADA # 141-061
Conditionally approved by FDA pending a full demonstration of effectiveness under application number 141-616.
It is a violation of Federal law to use this product other than as directed in the labeling.
Consult your veterinarian for assistance in the diagnosis, treatment, and control of parasitism.
Restricted Drug (CA) Use only as directed.
zoetis
Distributed by:
Zoetis Inc.
Kalamazoo, MI 49007
Product of China

Revised: August 2025

PRINCIPAL DISPLAY PANEL - 100 mL Multi-Dose Vial Label

Dectomax 100mL

PRINCIPAL DISPLAY PANEL - 250 mL Multi-Dose Vial Label

40054085

PRINCIPAL DISPLAY PANEL - 500 mL Multi-Dose Vial Label

40054086